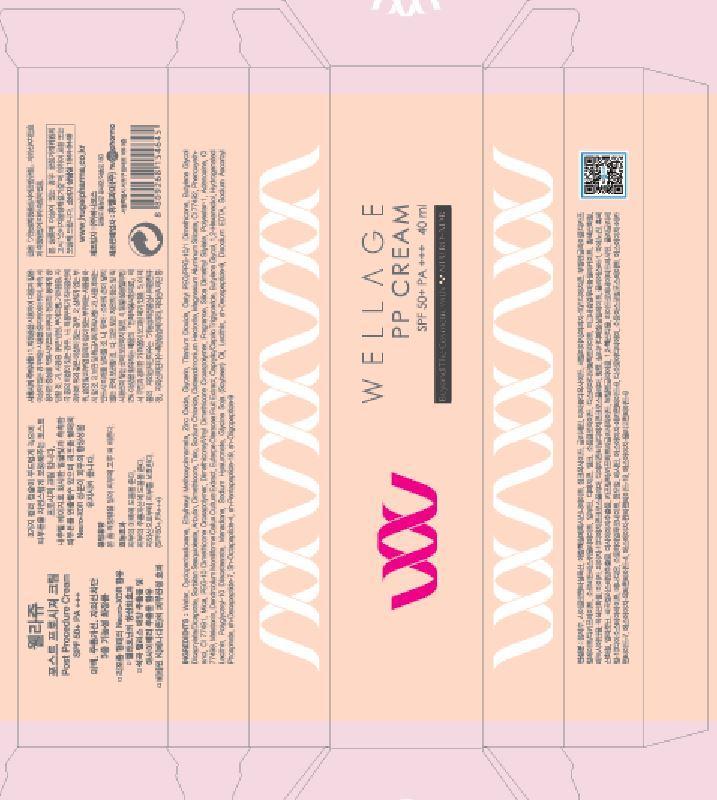 DRUG LABEL: WELLAGE POST PROCEDURE
NDC: 69346-1001 | Form: CREAM
Manufacturer: HUGEL PHARMA CO.,LTD.
Category: otc | Type: HUMAN OTC DRUG LABEL
Date: 20141101

ACTIVE INGREDIENTS: GLYCERIN 5 g/100 mL
INACTIVE INGREDIENTS: CYCLOMETHICONE 5; DIMETHICONE; ADENOSINE

Drug Facts

ACTIVE INGREDIENT

glycerin

INACTIVE INGREDIENT

water, cyclopentasiloxane, zinc oxide, titanium dioxide, arbutin, dimethicone, talc, sodium chloride, etc

PURPOSE

anti wrinkle
whitening
sun block

keep out or reach of the children

INDICATIONS AND USAGE

ake a proper amount and apply on the face evenly

Do not use in the following cases(Eczema and scalp wounds)
Due to the use of this druf if rash, irritation, itching and symptopms of hypersnesitivity occur dicontinue use and consult ypur phamacisr or doctor
If in contact with the eyes, wash out thoroughty with water If the symptoms are servere, seek medical advice immediately
This product is for exeternal use only. Do not use for internal use
Storage and handling precautions
If possible, avoid direct sunlight and store in cool and area of low humidity
In order to maintain the quality of the product and avoid misuse
Avoid placing the product near fire and store out in reach of children

DOSAGE AND ADMINISTRATION

for external use only